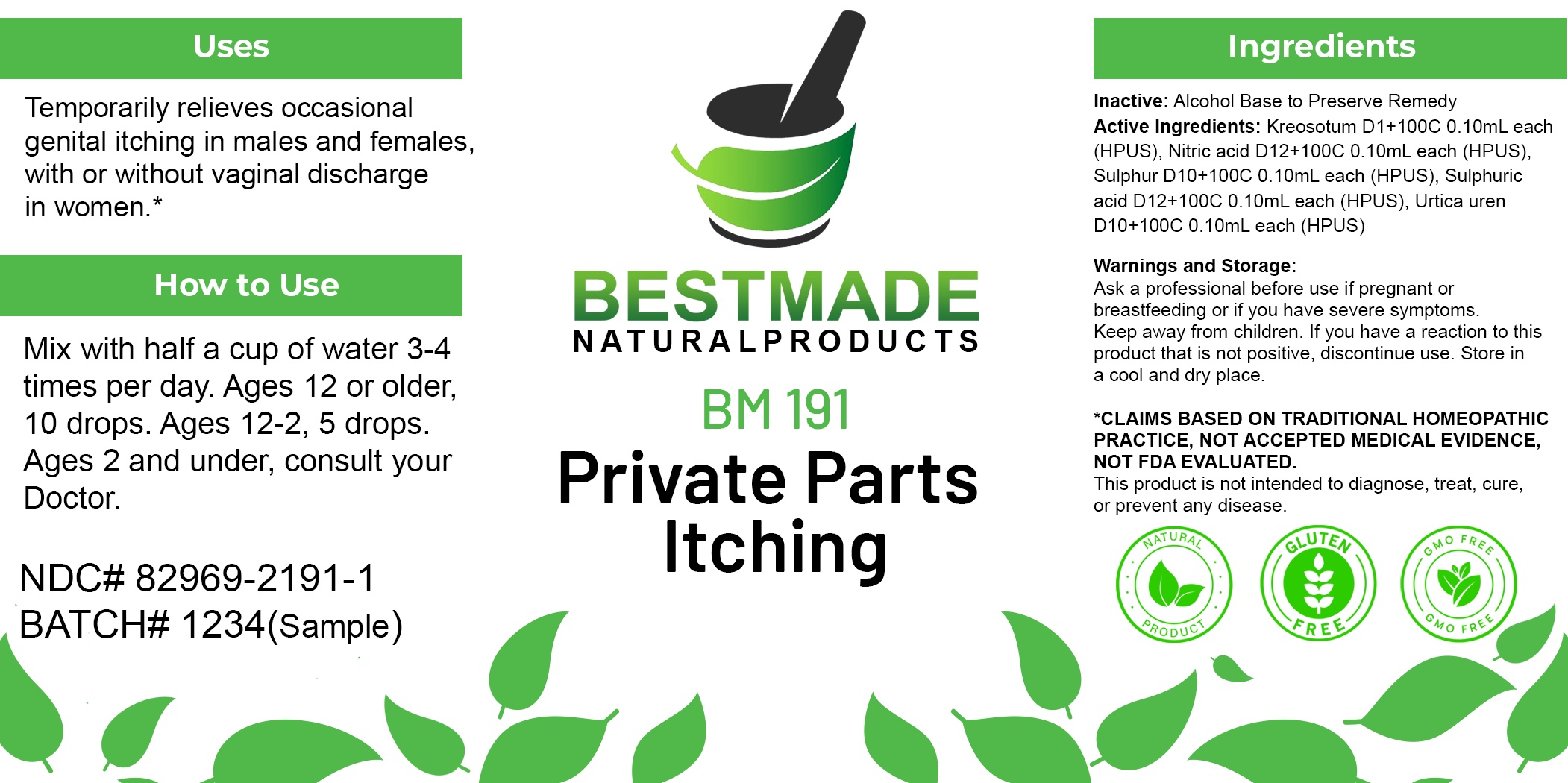 DRUG LABEL: Bestmade Natural Products BM191
NDC: 82969-2191 | Form: LIQUID
Manufacturer: Bestmade Natural Products
Category: homeopathic | Type: HUMAN OTC DRUG LABEL
Date: 20250221

ACTIVE INGREDIENTS: URTICA URENS 30 [hp_C]/30 [hp_C]; SULFURIC ACID 30 [hp_C]/30 [hp_C]; WOOD CREOSOTE 30 [hp_C]/30 [hp_C]; NITRIC ACID 30 [hp_C]/30 [hp_C]; SULFUR 30 [hp_C]/30 [hp_C]
INACTIVE INGREDIENTS: ALCOHOL 30 [hp_C]/30 [hp_C]

BM191

DOSAGE AND ADMINISTRATION

How to Use

Mix with half a cup of water 3-4 times per day. Ages 12 or older, 10 drops. Ages 12-2, 5 drops. Ages 2 and under, consult your Doctor.

Inactive:

Alcohol Base to Preserve Product

ACTIVE INGREDIENT

Active Ingredients: Kreosotum D1+100C 0.10mL each (HPUS), Nitric acid D12+100C 0.10mL each (HPUS), Sulphur D10+100C 0.10mL each (HPUS), Sulphuric acid D12+100C 0.10mL each (HPUS), Urtica uren D10+100C 0.10mL each (HPUS)

KEEP OUT OF REACH OF CHILDREN

Warnings and Storage:

Ask a professional before use if pregnant or breastfeeding or if you have severe symptoms.

Keep away from children. If you have a reaction to this product that is not positive, discontinue use. Store in a cool and dry place

*CLAIMS BASED ON TRADITIONAL HOMEOPATHIC PRACTICE, NOT ACCEPTED MEDICAL EVIDENCE NOT FDA EVALUATED.
This product is not intended to diagnose, treat, cure, or prevent any disease.

Warnings and Storage:

Ask a professional before use if pregnant or breastfeeding or if you have severe symptoms.

Keep away from children. If you have a reaction to this product that is not positive, discontinue use. Store in a cool and dry place

*CLAIMS BASED ON TRADITIONAL HOMEOPATHIC PRACTICE, NOT ACCEPTED MEDICAL EVIDENCE NOT FDA EVALUATED.
This product is not intended to diagnose, treat, cure, or prevent any disease.

Uses
Temporarily relieves occasional genital itching in males and females, with or without vaginal discharge in women.*

Uses
Temporarily relieves occasional genital itching in males and females, with or without vaginal discharge in women.*

Entire package label